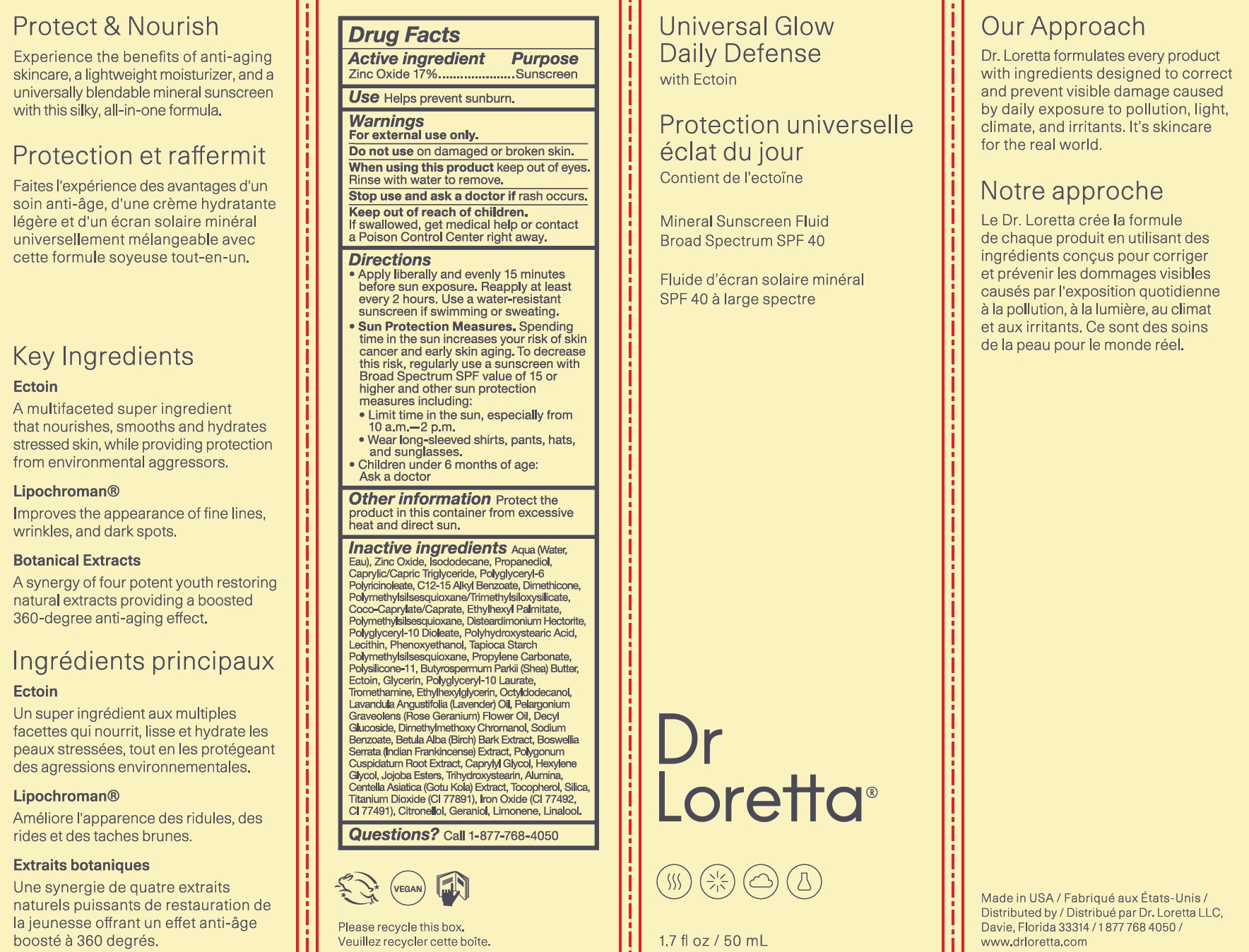 DRUG LABEL: Universal Glow Daily Defense SPF 40
NDC: 71501-1903 | Form: CREAM
Manufacturer: Dr. Loretta, LLC
Category: otc | Type: HUMAN OTC DRUG LABEL
Date: 20230504

ACTIVE INGREDIENTS: SALICYLIC ACID 170 mg/1 mL
INACTIVE INGREDIENTS: TROMETHAMINE; LAVENDER OIL; ALUMINUM OXIDE; ISODODECANE; MEDIUM-CHAIN TRIGLYCERIDES; DIMETHICONE; COCO-CAPRYLATE/CAPRATE; ETHYLHEXYL PALMITATE; POLYMETHYLSILSESQUIOXANE (4.5 MICRONS); DISTEARDIMONIUM HECTORITE; POLYGLYCERYL-10 DIOLEATE; POLYHYDROXYSTEARIC ACID (2300 MW); PHENOXYETHANOL; SHEA BUTTER; ECTOINE; GLYCERIN; ETHYLHEXYLGLYCERIN; DIMETHYLMETHOXY CHROMANOL; CENTELLA ASIATICA TRITERPENOIDS; FERRIC OXIDE RED; PROPANEDIOL; POLYGLYCERYL-6 POLYRICINOLEATE; PROPYLENE CARBONATE; PELARGONIUM GRAVEOLENS FLOWER OIL; HYDROGENATED JOJOBA OIL, RANDOMIZED; DIMETHICONE/VINYL DIMETHICONE CROSSPOLYMER (SOFT PARTICLE); OCTYLDODECANOL; INDIAN FRANKINCENSE; SILICON DIOXIDE; WATER; ALKYL (C12-15) BENZOATE; POLYMETHYLSILSESQUIOXANE/TRIMETHYLSILOXYSILICATE; LECITHIN, SUNFLOWER; POLYGLYCERYL-10 LAURATE; POLYGONUM CUSPIDATUM ROOT; TRIHYDROXYSTEARIN; TITANIUM DIOXIDE; FERRIC OXIDE YELLOW; STARCH, TAPIOCA; BETULA PUBESCENS BARK

Universal Glow Daily Defense SPF 40

ACTIVE INGREDIENT

Zinc Oxide 17%

PURPOSE

Sunscreen

Inactive Ingredients

Aqua (Water/Eau), Isododecane, Propanediol, Caprylic/Capric Triglyceride, Polyglyceryl-6 Polyricinoleate, C12-15 Alkyl Benzoate, Dimethicone, Polymethylsilsesquioxane/Trimethylsiloxysilicate, Coco-Caprylate/Caprate, Ethylhexyl Palmitate, Polymethylsilsesquioxane, Disteardimonium Hectorite, Polyglyceryl-10 Dioleate, Polyhydroxystearic Acid, Lecithin, Phenoxyethanol, Tapioca Starch Polymethylsilsesquioxane, Propylene Carbonate, Polysilicone-11, Butyrospermum Parkii (Shea) Butter, Ectoin, Glycerin, Polyglyceryl-10 Laurate, Tromethamine, Ethylhexylglycerin, Octyldodecanol, Lavandula Angustifolia (Lavender) Oil, Pelargonium Graveolens (Rose Geranium) Flower Oil, Decyl Glucoside, Dimethylmethoxy Chromanol, Sodium Benzoate, Betula Alba Bark Extract, Boswellia Serrata Extract, Polygonum Cuspidatum Root Extract, Caprylyl Glycol, Hexylene Glycol, Jojoba Esters, Trihydroxystearin, Alumina, Centella Asiatica Extract, Tocopherol, Silica, Titanium Dioxide (CI 77891), Iron Oxides (CI 77492, CI 77491).

WARNINGS

For external use only.

Do not use on damaged or broken skin.

When using this product keep out of eyes. Rinse with water to remove.

Stop and ask a doctor if rash occurs.

Keep out of reach of children. If swallowed, get medical help or contact a Poison Control Center right away.

DOSAGE AND ADMINISTRATION

Apply liberally and evenly 15 minutes before sun exposure. Reapply at last every 2 hours. Use a water-resistant sunscreen if swimming or sweating.

INDICATIONS AND USAGE

Helps prevent suburn